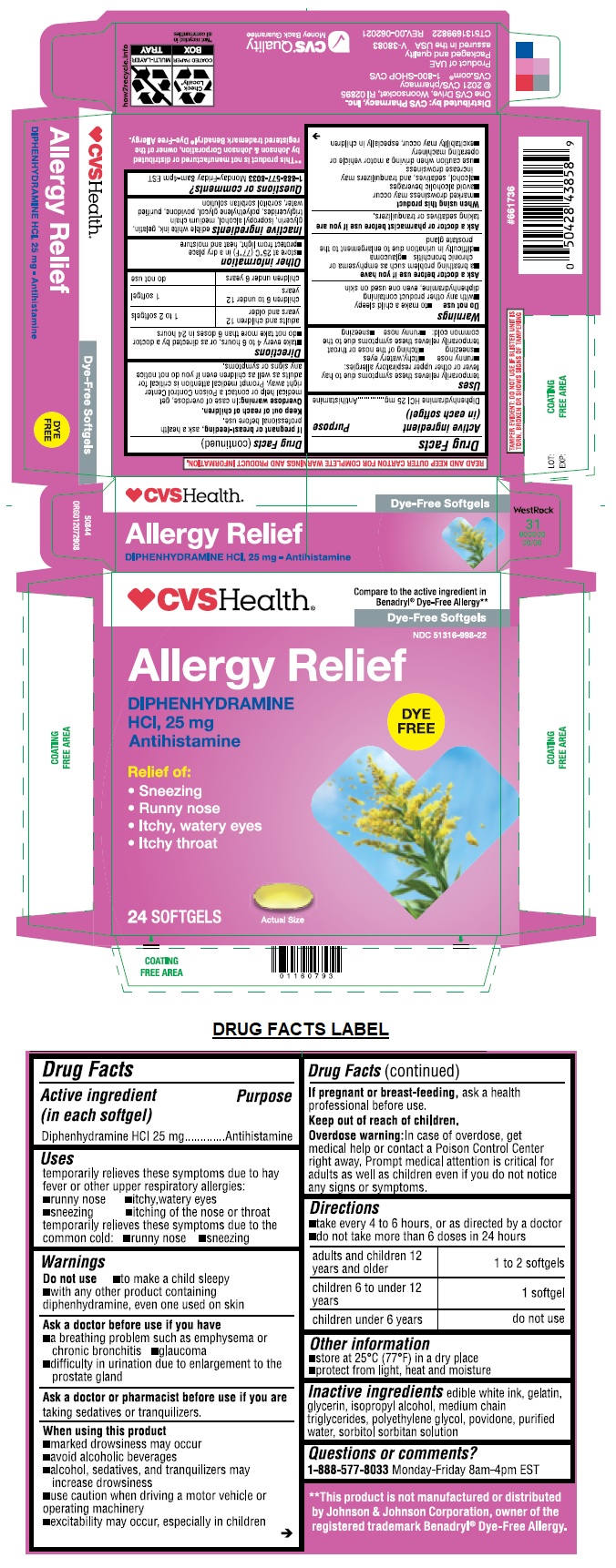 DRUG LABEL: Allergy Relief Dye-Free Softgel
NDC: 51316-998 | Form: CAPSULE, LIQUID FILLED
Manufacturer: CVS PHARMACY, INC
Category: otc | Type: HUMAN OTC DRUG LABEL
Date: 20241214

ACTIVE INGREDIENTS: DIPHENHYDRAMINE HYDROCHLORIDE 25 mg/1 1
INACTIVE INGREDIENTS: GELATIN, UNSPECIFIED; GLYCERIN; ISOPROPYL ALCOHOL; MEDIUM-CHAIN TRIGLYCERIDES; POLYETHYLENE GLYCOL, UNSPECIFIED; POVIDONE, UNSPECIFIED; WATER; SORBITOL; SORBITAN

Allergy Relief Dye-Free Softgel

Active ingredients (in each softgel)

Diphenhydramine HCl 25 mg

Purpose

Antihistamine

Uses

temporarily relieves these symptoms due to hay fever or other upper respiratory allergies:
• runny nose • itchy, watery eyes
• sneezing • itching of the nose or throat
temporarily relieves these symptoms due to the common cold: • runny nose • sneezing

Warnings

Do not use • to make a child sleepy • with any other product containing diphenhydramine, even one used on skin

Ask a doctor before use if you have • a breathing problem such as emphysema or chronic bronchitis • glaucoma • difficulty in urination due to enlargement to the prostate gland

Ask a doctor or pharmacist before use if you are taking sedatives or tranquilizers.

When using this product
• marked drowsiness may occur
• avoid alcoholic beverages
• alcohol, sedatives, and tranquilizers may increase drowsiness
• use caution when driving a motor vehicle or operating machinery
• excitability may occur, especially in children

If pregnant or breast-feeding, ask a health professional before use.

Keep out of reach of children.

Overdose warning: In case of overdose, get medical help or contact a Poison Control Center right away. Prompt medical attention is critical for adults as well as children even if you do not notice any signs or symptoms.

Directions

• take every 4 to 6 hours, or as directed by a doctor
• do not take more than 6 doses in 24 hours

adults and children 12 years and older | 1 to 2 softgels
children 6 to under 12 years | 1 softgel
children 6 under years | do not use

Other information

• store at 25°C (77°F) in a dry place
• protect from light, heat and moisture

Inactive ingredients

gelatin, glycerin, isopropyl alcohol, medium chain triglycerides, polyethylene glycol, povidone, purified water, sorbitol sorbitan solution, white ink

Questions or comments?

1-888-577-8033 Monday-Friday 9am-4:30pm EST

Compare to the active ingredients in Benadryl® Dye-Free Allergy LIQUID-GELS®*

RELIEF OF:
• SNEEZING
• RUNNY NOSE
• ITCHY, WATERY EYES
• ITCHY THROAT

READ AND KEEP OUTER PACKAGE FOR COMPLETE PRODUCT INFORMATION

*This product is not manufactured or distributed by Johnson&Johnson Corporation, owner of the registered trademark Benadryl® Dye-Free Allergy LIQUID GELS®

Product of UAE
Packaged and Quality Assured in the USA

TAMPER EVIDENT: DO NOT USE IF BLISTER UNIT IS TORN, BROKEN OR SHOWS SIGNS OF TAMPERING

Distributed by: CVS Pharmacy, Inc.One CVS Drive, Woonsocket, RI 02895
© 2021 CVS/pharmacy
CVS.com® 1-800-SHOP CVS